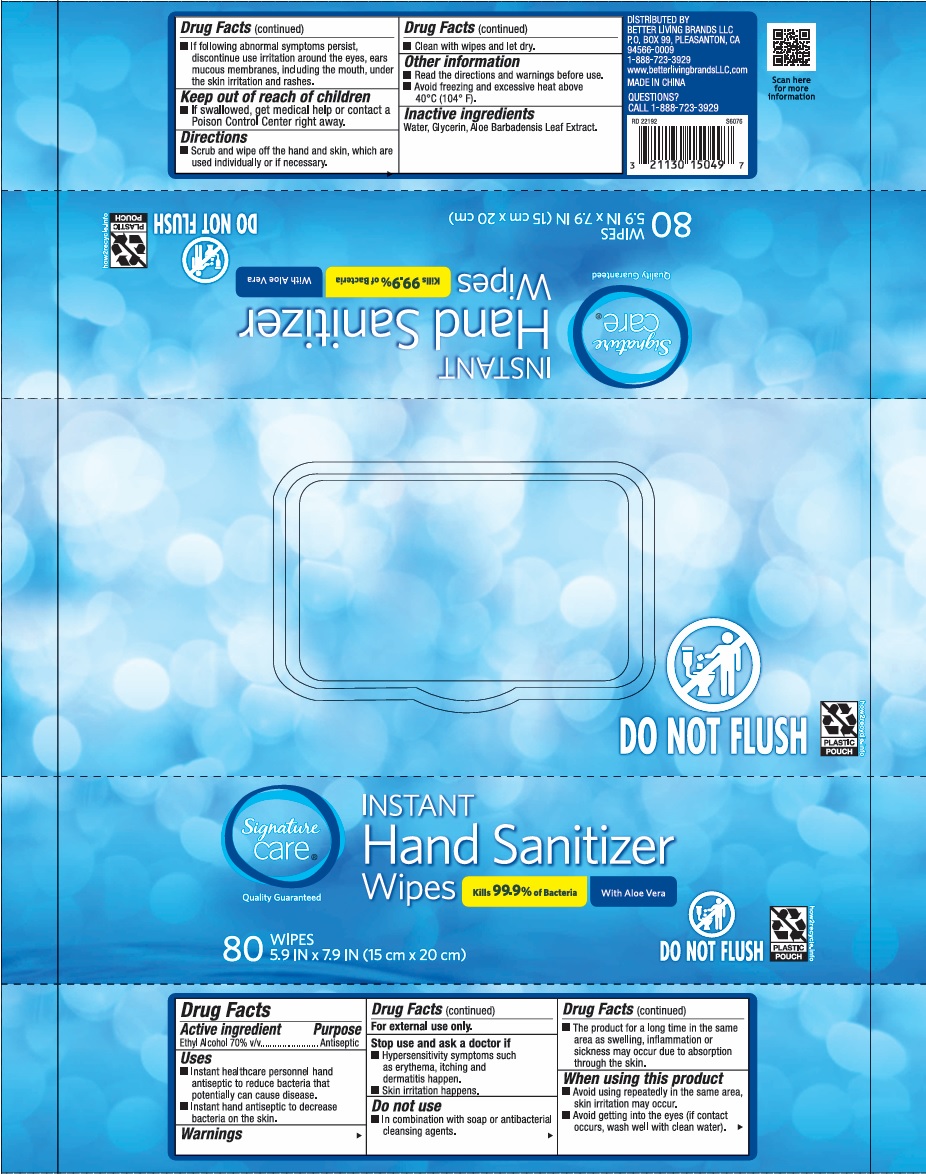 DRUG LABEL: Signature Care Instant Hand Sanitizizer Wipes
NDC: 74149-112 | Form: SWAB
Manufacturer: Yiwu Yangjie Daily Chemicals Co.,Ltd.
Category: otc | Type: HUMAN OTC DRUG LABEL
Date: 20250311

ACTIVE INGREDIENTS: ALCOHOL 70 g/100 g
INACTIVE INGREDIENTS: WATER; GLYCERIN; ALOE BARBADENSIS LEAF JUICE

Ethyl Alcohol Wipes

Active Ingredient

Ethyl Alcohol 70% v/v

Purpose

Antiseptic

USE

- Instant healthcare personnel hand antiseptic to reduce bacteria that potentially can cause disease.
- Instant hand antiseptic to decrease bacteria on the skin.

Warning

- For external use only.

Stop use and ask a doctor if

- Hypersensitivity symptoms suchas erythema, itching and dermatitis happen.
- Skin irritation happens.
- If dollowing avnomal symptoms persist, discontinue use irritation around the eyes, ears mucous membranes, including the mouth, under the skin irritation and rashes.

Other Information:

- Read the directions and warning before use
- Avoid freezing and excessive heat above 40℃ （104℉）.

KEEP OUT OF REACH OF CHILDREN

●If swallowed, get medical help or contact a Poison Contrl Center right away.

Directions

- Clean with wipes and let dry.

Inactive ingredients

water, glycerin, alow barbadensis leaf extract